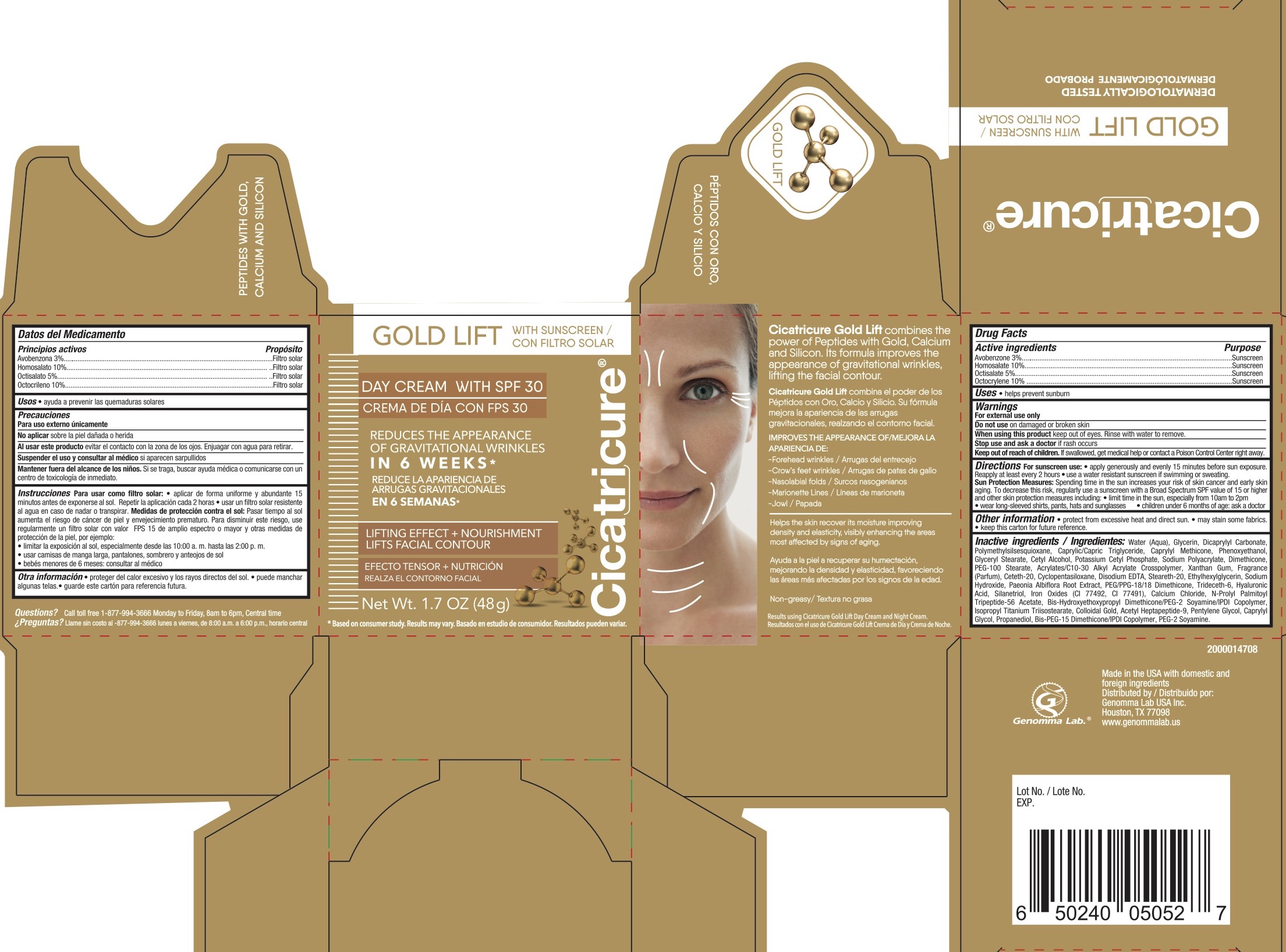 DRUG LABEL: Cicatricure Gold Lift SPF 30 Sunscreen
NDC: 50066-181 | Form: LOTION
Manufacturer: Genomma Lab USA
Category: otc | Type: HUMAN OTC DRUG LABEL
Date: 20250510

ACTIVE INGREDIENTS: HOMOSALATE 10 g/100 g; AVOBENZONE 3 g/100 g; OCTOCRYLENE 10 g/100 g; OCTISALATE 5 g/100 g
INACTIVE INGREDIENTS: ETHYLHEXYLGLYCERIN; GLYCERYL STEARATE; CAPRYLYL METHICONE; CETYL ALCOHOL; PEG-100 STEARATE; SODIUM HYDROXIDE; PAEONIA LACTIFLORA ROOT; ACETYL HEPTAPEPTIDE-4; POLYMETHYLSILSESQUIOXANE (11 MICRONS); STEARETH-20; SILANETRIOL; CAPRYLYL GLYCOL; SODIUM POLYACRYLATE (8000 MW); ACRYLATES/C10-30 ALKYL ACRYLATE CROSSPOLYMER (60000 MPA.S); CETETH-20; CYCLOPENTASILOXANE; EDETATE DISODIUM; XANTHAN GUM; PEG/PPG-18/18 DIMETHICONE; HYALURONIC ACID; CI 77492; CI 77491; CALCIUM CHLORIDE; PENTYLENE GLYCOL; N-PROLYL PALMITOYL TRIPEPTIDE-56 ACETATE; COLLOIDAL GOLD; PROPANEDIOL; DIMETHICONE 200; PHENOXYETHANOL; POTASSIUM CETYL PHOSPHATE; CASTOR OIL/IPDI COPOLYMER; ISOPROPYL TITANIUM TRIISOSTEARATE; GLYCERIN; DICAPRYLYL CARBONATE; CAPRYLIC/CAPRIC TRIGLYCERIDE; TRIDECETH-6; WATER

ACTIVE INGREDIENT

Avobenzone 3%, Homosalate 10%, Octisalate 5%, Ocrocrylene 10%

PURPOSE

Sunscreen

INDICATIONS AND USAGE

Helps prevent sunscreen

WARNINGS

For external use only.

Do not use on damaged or broken skin.

When using this product keep out of eyes. Rinse with water to remove.

Stop use and ask a doctor if rash occurs.

KEEP OUT OF REACH OF CHILDREN

If swallowed, get medical help or contact a Poison Control Center right away.

DOSAGE AND ADMINISTRATION

For sunscreen use:

Apply liberally 15 minutes before sun exposure. Reapply at least every 2 hours, use a water resistant sunscreen if swimming or sweating. Sun protection measures: spending time in the sun increases your risk of skin cancer and early skin aging. To decrease risk, regularly use a sunscreen with broad spectrum SPF of 15 or higher and other sun protection measure including:

limit time in the sun, especially from 10 am to 2 pm
wear long-sleeved shirts, pants, hats, and sunglasses.
Children under 6 months: ask a doctor.

INACTIVE INGREDIENT

Water, Glycerin, Dicaprylyl Carbonate, Polymethylsilsesquioxane, Caprylic/Capric Triglyerice, Caprylyl Mthicone, Phenoxyethanol, Glyceryl Stearate, Cetyl Alcohol, Potassium Cetyl Phosphate, Sodium Polyacrylate, Dimethicone, PEG-100 Stearate, Acrylates/C10-30 Alkyl Acrylate Crosspolymer, Xanthan Gum, Fragrance, Ceteth-20, Cyclopentasiloxane, Disodium EDTA, Steareth-20, Ethylhexylglycerin, Sodium Hydroxide, Paeonia Albiflora Root Extract, PEG/PPG-18/19 Dimethicone, Trideceth-6, Hyaluronic Acid, Silanetriol, Iron Oxides (CI 77492, CI 77491), Calcium Chloride, N-Propyl Palmitoyl Tripeptide-56 Acetate, Bis-Hydroxyethoxypropyl Dimethicone/PEG-2 Soyamine/IPDI Copolymer, Isopropyl Titanium Triisostearate, Colloidal Gold, Acetyl Heptapeptide-9, Pentylene Glycol, Caprylyl Glycol, Propanediol, Bid-PEG-15 Dimethicon/IPDI Copolymer, PEG-2 Soyamine.